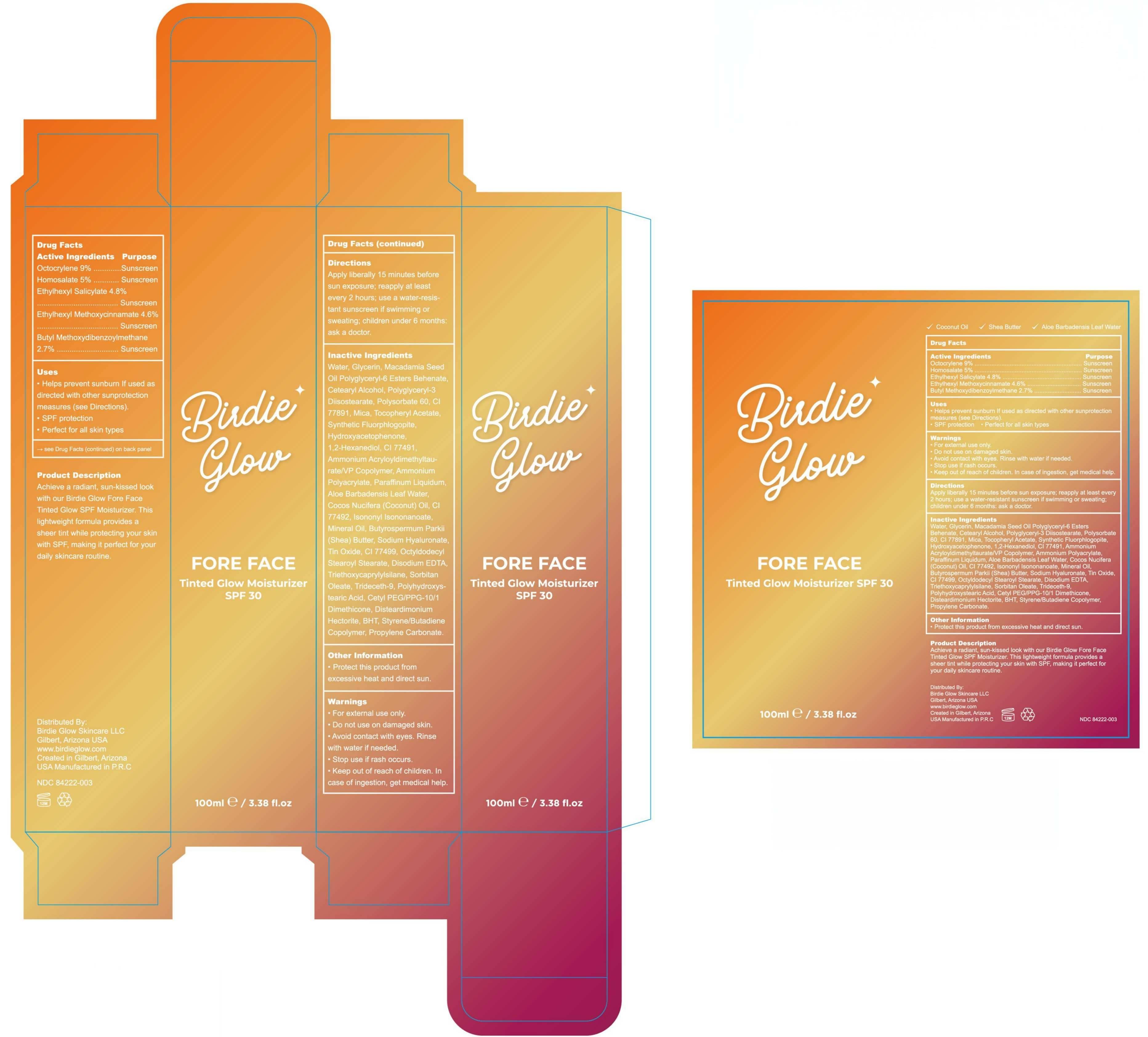 DRUG LABEL: Birdie Glow Tinted Glow Moisturizer SPF 30
NDC: 84222-003 | Form: LOTION
Manufacturer: Foshan Miwei Cosmetics Co., Ltd.
Category: otc | Type: HUMAN OTC DRUG LABEL
Date: 20250928

ACTIVE INGREDIENTS: AVOBENZONE 2.7 g/100 mL; OCTOCRYLENE 9 g/100 mL; HOMOSALATE 5 g/100 mL; ETHYLHEXYL SALICYLATE 4.8 g/100 mL; OCTINOXATE 4.6 g/100 mL
INACTIVE INGREDIENTS: TRIDECETH-9 0.0225 mL/100 mL; LIGHT MINERAL OIL 0.1125 mL/100 mL; SORBITAN OLEATE 0.0225 mL/100 mL; OCTYLDODECYL STEAROYL STEARATE 0.06 mL/100 mL; GLYCERIN 5 mL/100 mL; CETEARYL ALCOHOL 2 mL/100 mL; CETYL PEG/PPG-10/1 DIMETHICONE (HLB 5) 0.0135 mL/100 mL; ISONONYL ISONONANOATE 0.1435 mL/100 mL; TIN OXIDE 0.1 mL/100 mL; EDETATE DISODIUM 0.05 mL/100 mL; DISTEARDIMONIUM HECTORITE 0.0063 mL/100 mL; BHT 0.0046 mL/100 mL; PROPYLENE CARBONATE 0.0014 mL/100 mL; METHACRYLATE/METHOXY PEG-10 MALEATE/STYRENE COPOLYMER 0.002 mL/100 mL; SODIUM HYALURONATE 0.1 mL/100 mL; CI 77499 0.07 mL/100 mL; POLYHYDROXYSTEARIC ACID (2300 MW) 0.0185 mL/100 mL; TRIETHOXYCAPRYLYLSILANE 0.0228 mL/100 mL; 1,2-HEXANEDIOL 0.5 mL/100 mL; COCONUT OIL 0.2 mL/100 mL; ALOE VERA LEAF 0.2 mL/100 mL; CI 77891 1.95 mL/100 mL; WATER 51.0125 mL/100 mL; SHEA BUTTER 0.1 mL/100 mL; MICA 1.8 mL/100 mL; .ALPHA.-TOCOPHEROL ACETATE 1 mL/100 mL; MAGNESIUM POTASSIUM ALUMINOSILICATE FLUORIDE 0.85 mL/100 mL; HYDROXYACETOPHENONE 0.5 mL/100 mL; CI 77491 0.37 mL/100 mL; AMMONIUM ACRYLOYLDIMETHYLTAURATE/VP COPOLYMER 0.3 mL/100 mL; POLYGLYCERYL-3 DIISOSTEARATE 2 mL/100 mL; CI 77492 0.162 mL/100 mL; SODIUM POLYACRYLATE (8000 MW) 0.27 mL/100 mL; PARAFFINUM LIQUIDUM 0.24 mL/100 mL; POLYSORBATE 60 2 mL/100 mL; POLYGLYCERYL-6 BEHENATE 2.7 mL/100 mL

Birdie Glow Tinted Glow Moisturizer SPF 30

ACTIVE INGREDIENT

Octocrylene 9%

Homosalate 5%

Ethylhexyl Salicylate 4.8%

Ethylhexyl Methoxycinnamate 4.5954%.

Butyl Methoxydibenzoylmethane 2.7%

PURPOSE

Sunscreen

Uses

Helps prevent sunburn, decreases the risk of skin cancer and early skin aging if used as directed.

SPF protection

Perfect for all skin types

DESCRIPTION

Achieve a radiant, sun-kissed look with our Birdie Glow Fore Face Tinted Glow SPF Moisturizer. This lightweight formula provides a sheer tint while protecting your skin with SPF, making it perfect for your daily skincare routine.

DOSAGE AND ADMINISTRATION

Apply liberally 15 minutes before
sun exposure; reapply at least
every 2 hours; use a water-resis-
tant sunscreen if swimming or
sweating; children under 6 months:
ask a doctor.

INACTIVE INGREDIENT

Water, Glycerin, Macadamia Seed Oil Polyglyceryl-6 Esters Behenate, Cetearyl Alcohol, Polyglyceryl-3 Diisostearate, Polysorbate 60, CI 77891, Mica, Tocopheryl Acetate, Synthetic Fluorphlogopite, Hydroxyacetophenone, 1,2-Hexanediol, CI 77491, Ammonium Acryloyldimethyltaurate/VP Copolymer, Ammonium Polyacrylate, Paraffinum Liquidum, Aloe Barbadensis Leaf Water, Cocos Nucifera (Coconut) Oil, CI 77492, Isononyl Isononanoate, Mineral Oil, Butyrospermum Parkii (Shea) Butter, Sodium Hyaluronate, Tin Oxide, CI 77499, Octyldodecyl Stearoyl Stearate, Disodium EDTA, Triethoxycaprylylsilane, Sorbitan Oleate, Trideceth-9, Polyhydroxystearic Acid, Cetyl PEG/PPG-10/1 Dimethicone, Disteardimonium Hectorite, BHT, Styrene/Butadiene Copolymer, Propylene Carbonate

Warnings

· For external use only.

· Do not use on damaged skin.

· Avoid contact with eyes. Rinse with water if needed.

· Stop use if rash occurs.

· Keep out of reach of children. In case of ingestion, get medical help.

Other information

· Protect this product from excessive heat and direct sun.

· Keep out of reach of children. In case of ingestion, get medical help.

RECENT MAJOR CHANGES

Indications & Usage

Updated indication wording for clarity (no change in therapeutic intent).

Dosage and Administration

Updated direction wording for clarity (no change in therapeutic intent).